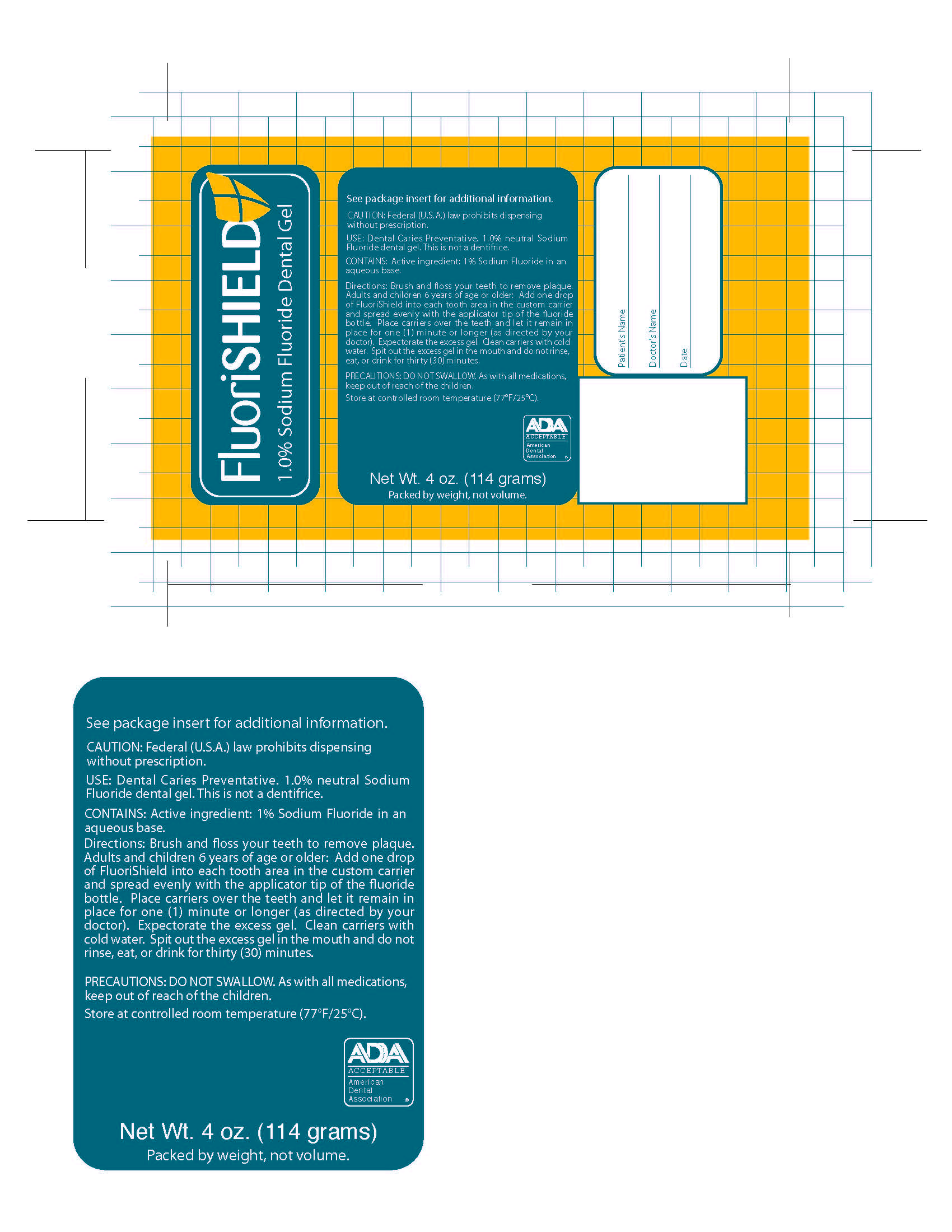 DRUG LABEL: FLUORISHIELD
NDC: 0273-8011 | Form: GEL
Manufacturer: Young Dental Manufacturing I, LLC
Category: prescription | Type: HUMAN PRESCRIPTION DRUG LABEL
Date: 20181213

ACTIVE INGREDIENTS: Sodium Fluoride 11 mg/1 g
INACTIVE INGREDIENTS: SACCHARIN SODIUM; HYDROXYETHYL CELLULOSE (4000 MPA.S AT 1%)

Inactives

Natrosol 250 (Hydroxyethyl Cellulose), Saccharin Sodium

Warning:

PRECAUTIONS: DO NOT SWALLOW. As with all medications, keep out of reach of the children

Directions

Brush and floss your teeth to remove plaque. Adults and children 6 years of age or older: Add one drop of FluoriShield into each tooth area in the custom carrier and spread evenly with the applicator tip of the fluoride bottle. Place carriers over the teeth and let it remain in place for one (1) minute or longer (as directed by your doctor). Expectorate the excess gel. Clean carriers with cold water. Spit out the excess gel in the mouth and do not rinse, eat, or drink for thirty (30) minutes.